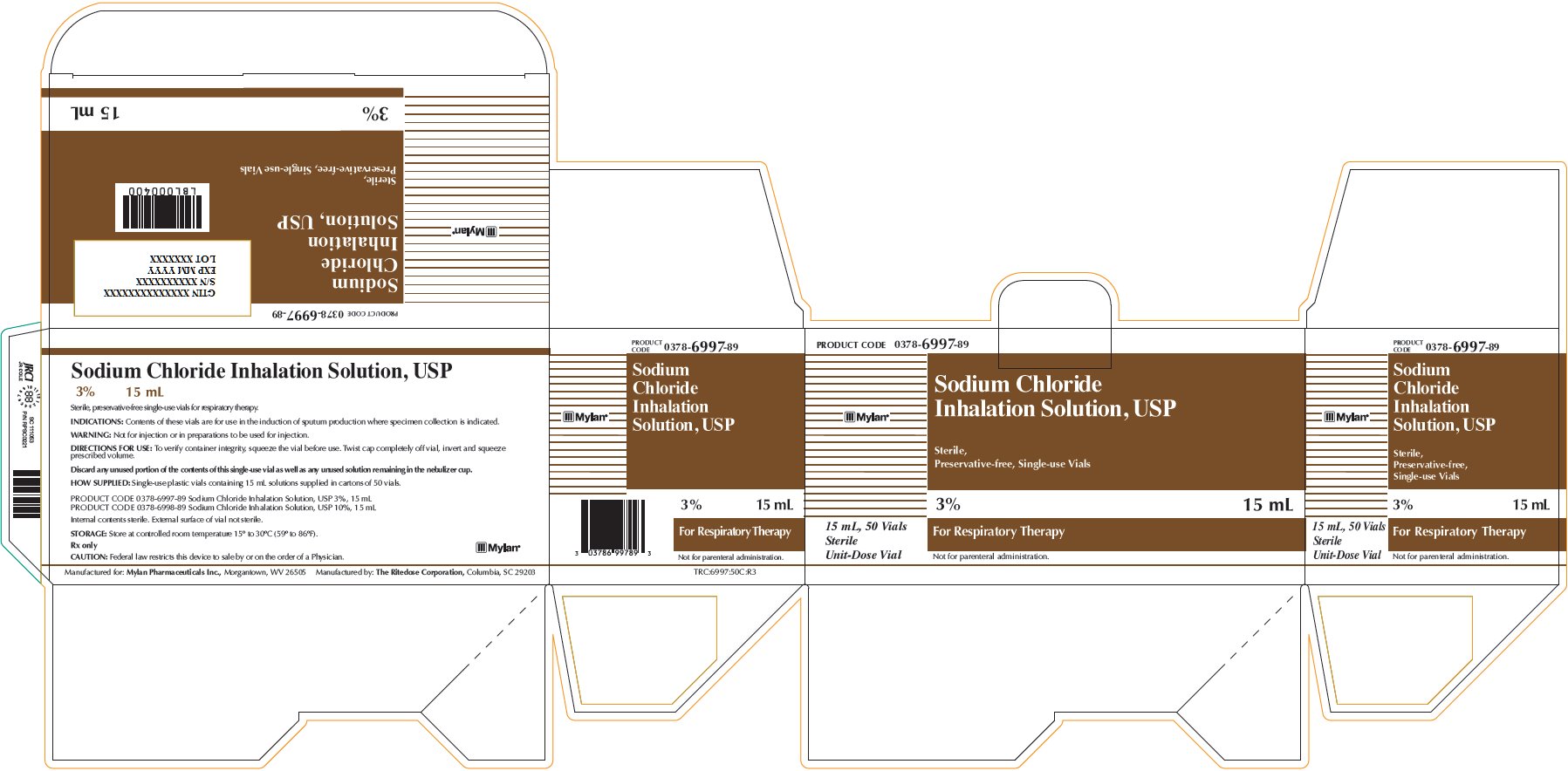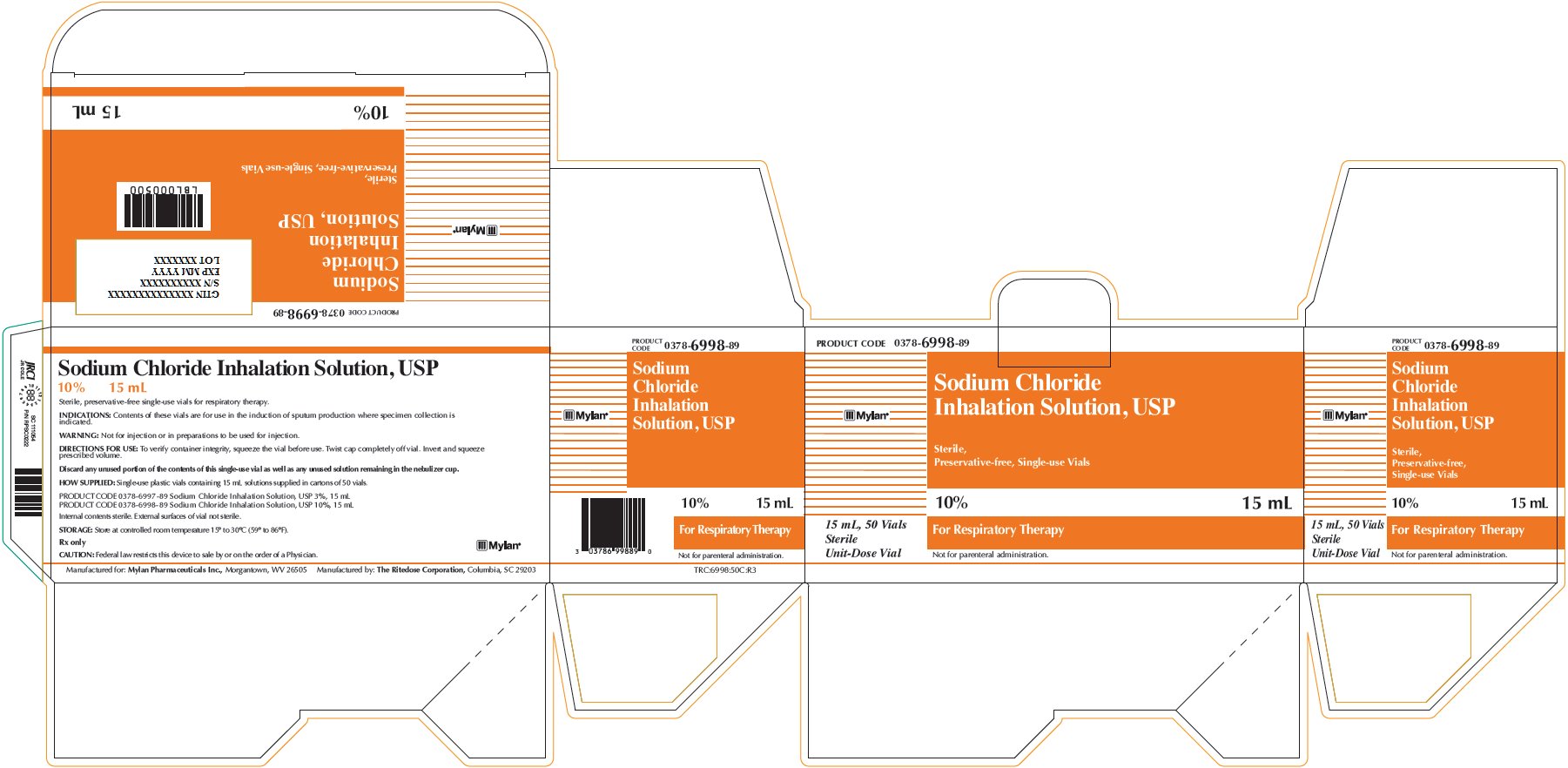 DRUG LABEL: Sodium Chloride
NDC: 0378-6997
Manufacturer: Mylan Pharmaceuticals Inc.
Category: other | Type: MEDICAL DEVICE
Date: 20171020

ACTIVE INGREDIENTS: SODIUM CHLORIDE 0.45 g/15 mL

Sodium Chloride Inhalation Solution 3% 15 mL

PRODUCT CODE 0378-6997-89

Sodium Chloride
Inhalation Solution, USP
Sterile,
Preservative-free, Single-use Vials

3% 15 mL

For Respiratory Therapy

Not for parenteral administration.

15 mL, 50 Vials
Sterile
Unit-Dose Vial

Sodium Chloride Inhalation Solution, USP
3% 15 mL

Sterile, preservative-free single-use vials for respiratory therapy.

INDICATIONS: Contents of these vials are for use in the induction of sputum production where specimen collection is indicated.

WARNING: Not for injection or in preparations to be used for injection.

DIRECTIONS FOR USE: To verify container integrity, squeeze the vial before use. Twist cap completely off vial, invert and squeeze prescribed volume.

Discard any unused portion of the contents of this single-use vial as well as any unused solution remaining in the nebulizer cup.

HOW SUPPLIED: Single-use plastic vials containing 15 mL solutions supplied in cartons of 50 vials.

PRODUCT CODE 0378-6997-89 Sodium Chloride Inhalation Solution, USP 3%, 15 mL
PRODUCT CODE 0378-6998-89 Sodium Chloride Inhalation Solution, USP 10%, 15 mL

Internal contents sterile. External surface of vial not sterile.

STORAGE: Store at controlled room temperature 15° to 30°C (59° to 86°F).

Rx only

CAUTION: Federal law restricts this device to sale by or on the order of a Physician.

Manufactured for: Mylan Pharmaceuticals Inc., Morgantown, WV 26505 Manufactured by: The Ritedose Corporation, Columbia, SC 26203

TRC:6997:50C:R3

Sodium Chloride Inhalation Solution 10% 15 mL

PRODUCT CODE 0378-6998-89

Sodium Chloride
Inhalation Solution, USP

Sterile,
Preservative-free, Single-use Vials
10% 15 mL

For Respiratory Therapy

Not for parenteral administration.

15 mL, 50 Vials
Sterile
Unit-Dose Vial

Sodium Chloride Inhalation Solution, USP
10% 15 mL

Sterile, preservative-free single-use vials for respiratory therapy.

INDICATIONS: Contents of these vials are for use in the induction of sputum production where specimen collection is indicated.

WARNING: Not for injection or in preparations to be used for injection.

DIRECTIONS FOR USE: To verify container integrity, squeeze the vial before use. Twist cap completely off vial. Invert and squeeze prescribed volume.

Discard any unused portion of the contents of this single-use vial as well as any unused solution remaining in the nebulizer cup.

HOW SUPPLIED: Single-use plastic vials containing 15 mL solutions supplied in cartons of 50 vials.

PRODUCT CODE 0378-6997-89 Sodium Chloride Inhalation Solution, USP 3%, 15 mL
PRODUCT CODE 0378-6998-89 Sodium Chloride Inhalation Solution, USP 10%, 15 mL

Internal contents sterile. External surface of vial not sterile.

STORAGE: Store at controlled room temperature 15° to 30°C (59° to 86°F).

Rx only

CAUTION: Federal law restricts this device to sale by or on the order of a Physician.

Manufactured for: Mylan Pharmaceuticals Inc., Morgantown, WV 26505 Manufactured by: The Ritedose Corporation, Columbia, SC 26203

TRC:6998:50C:R3